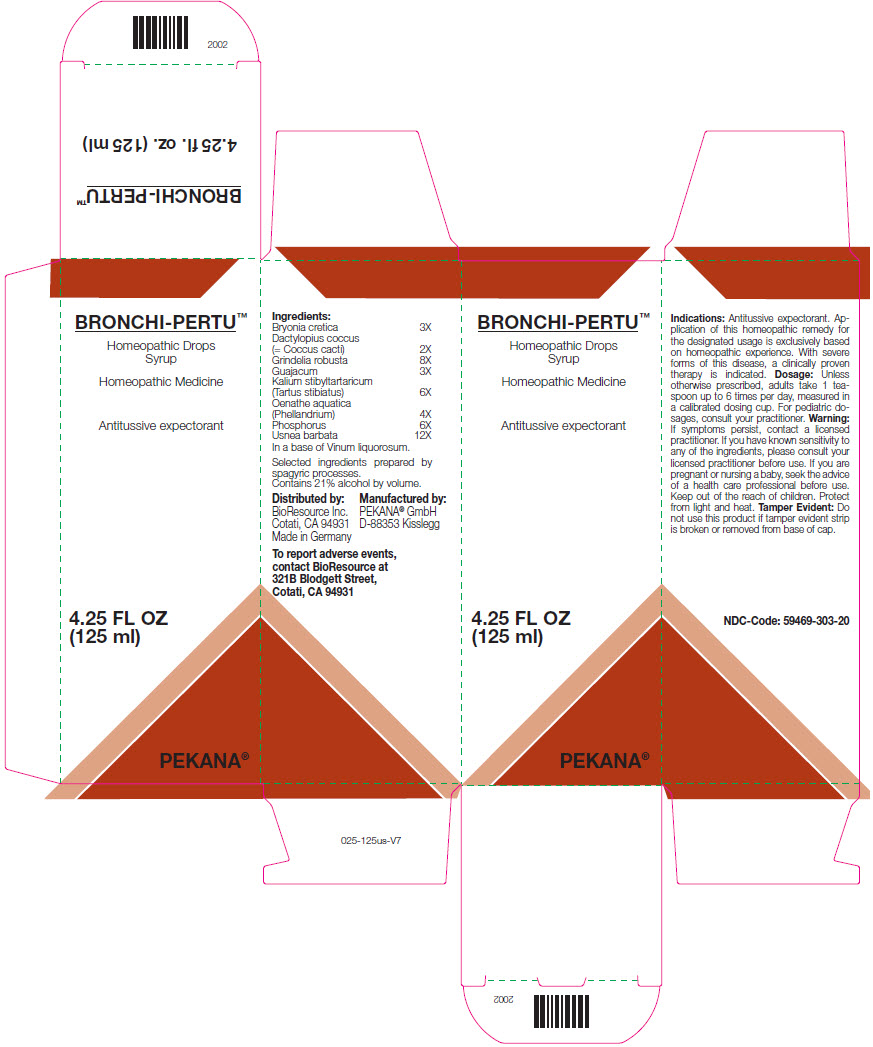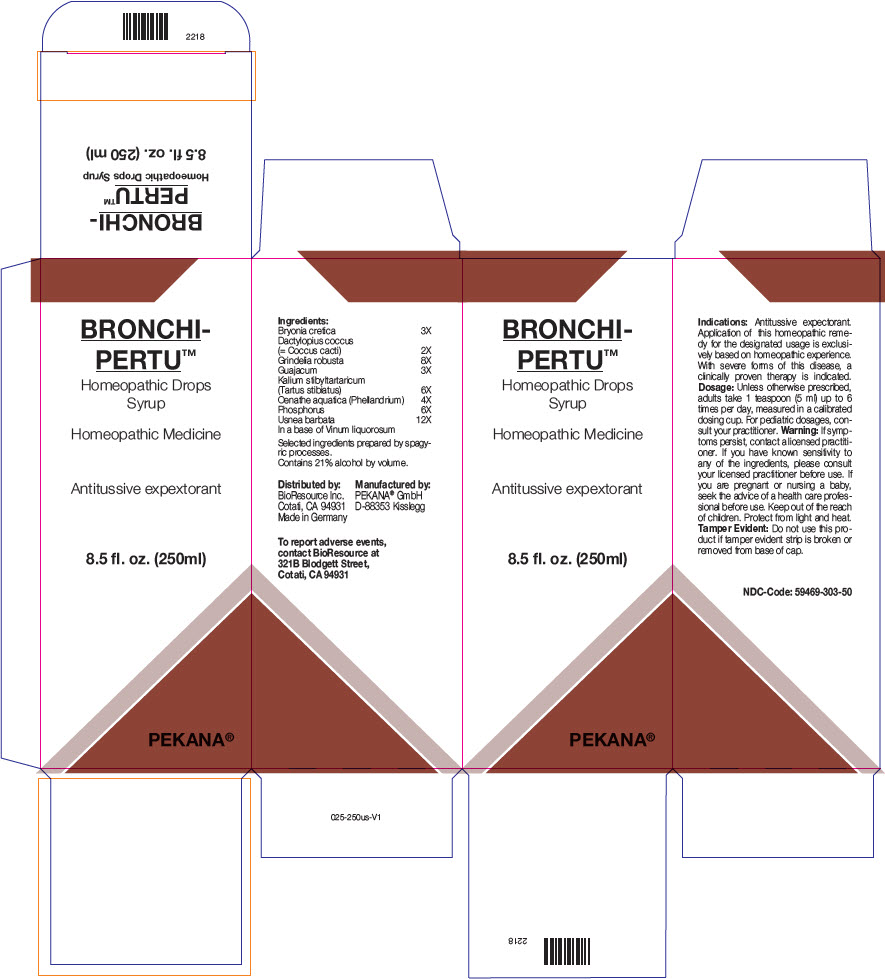 DRUG LABEL: BRONCHI-PERTU
NDC: 59469-303 | Form: SYRUP
Manufacturer: PEKANA Naturheilmittel GmbH
Category: homeopathic | Type: HUMAN OTC DRUG LABEL
Date: 20221223

ACTIVE INGREDIENTS: BRYONIA DIOICA ROOT 3 [hp_X]/125 mL; PROTORTONIA CACTI 2 [hp_X]/125 mL; GUAIACUM OFFICINALE RESIN 3 [hp_X]/125 mL; OENANTHE AQUATICA FRUIT 4 [hp_X]/125 mL; PHOSPHORUS 6 [hp_X]/125 mL; ANTIMONY POTASSIUM TARTRATE 6 [hp_X]/125 mL; USNEA BARBATA 12 [hp_X]/125 mL; GRINDELIA HIRSUTULA WHOLE 8 [hp_X]/125 mL
INACTIVE INGREDIENTS: WATER; ALCOHOL

BRONCHI-PERTU™

ACTIVE INGREDIENT

Ingredients:
Bryonia cretica | 3X
Dactylopius coccus (= Coccus cacti) | 2X
Grindelia robusta | 8X
Guajacum | 3X
Kalium stibyltartaricum (Tartus stibiatus) | 6X
Oenathe aquatica (Phellandrium) | 4X
Phosphorus | 6X
Usnea barbata | 12X

In a base of Vinum liquorosum.

Selected ingredients prepared by spagyric processes.

INACTIVE INGREDIENT

Contains 21% alcohol by volume.

Indications

PURPOSE

Antitussive expextorant. Application of this homeopathic remedy for the designated usage is exclusively based on homeopathic experience. With severe forms of this disease, a clinically proven therapy is indicated.

Dosage

Unless otherwise prescribed, adults take 1 teaspoon up to 6 times per day, measured in a calibrated dosing cup. For pediatric dosages, consult your practitioner.

Warning

ASK DOCTOR

If symptoms persist, contact a licensed practitioner. If you have known sensitivity to any of the ingredients, please consult your licensed practitioner before use.

If you are pregnant or nursing a baby, seek the advice of a health care professional before use.

Keep out of the reach of children.

STORAGE AND HANDLING

Protect from light and heat.

Tamper Evident

Do not use this product if tamper evident strip is broken or removed from base of cap.

QUESTIONS

To report adverse events, contact BioResource at 321B Blodgett Street, Cotati, CA 94931

Distributed by:
BioResource Inc.
Cotati, CA 94931

Manufactured by:
PEKANA® GmbH
D-88353 Kisslegg

PRINCIPAL DISPLAY PANEL - 125 ml Bottle Box

BRONCHI-PERTU™

Homeopathic Drops
Syrup

Homeopathic Medicine

Antitussive expectorant

4.25 FL OZ
(125 ml)

PEKANA®

PRINCIPAL DISPLAY PANEL - 250 ml Bottle Box

BRONCHI-
PERTU™

Homeopathic Drops
Syrup

Homeopathic Medicine

Antitussive expextorant

8.5 fl. oz. (250ml)

PEKANA®